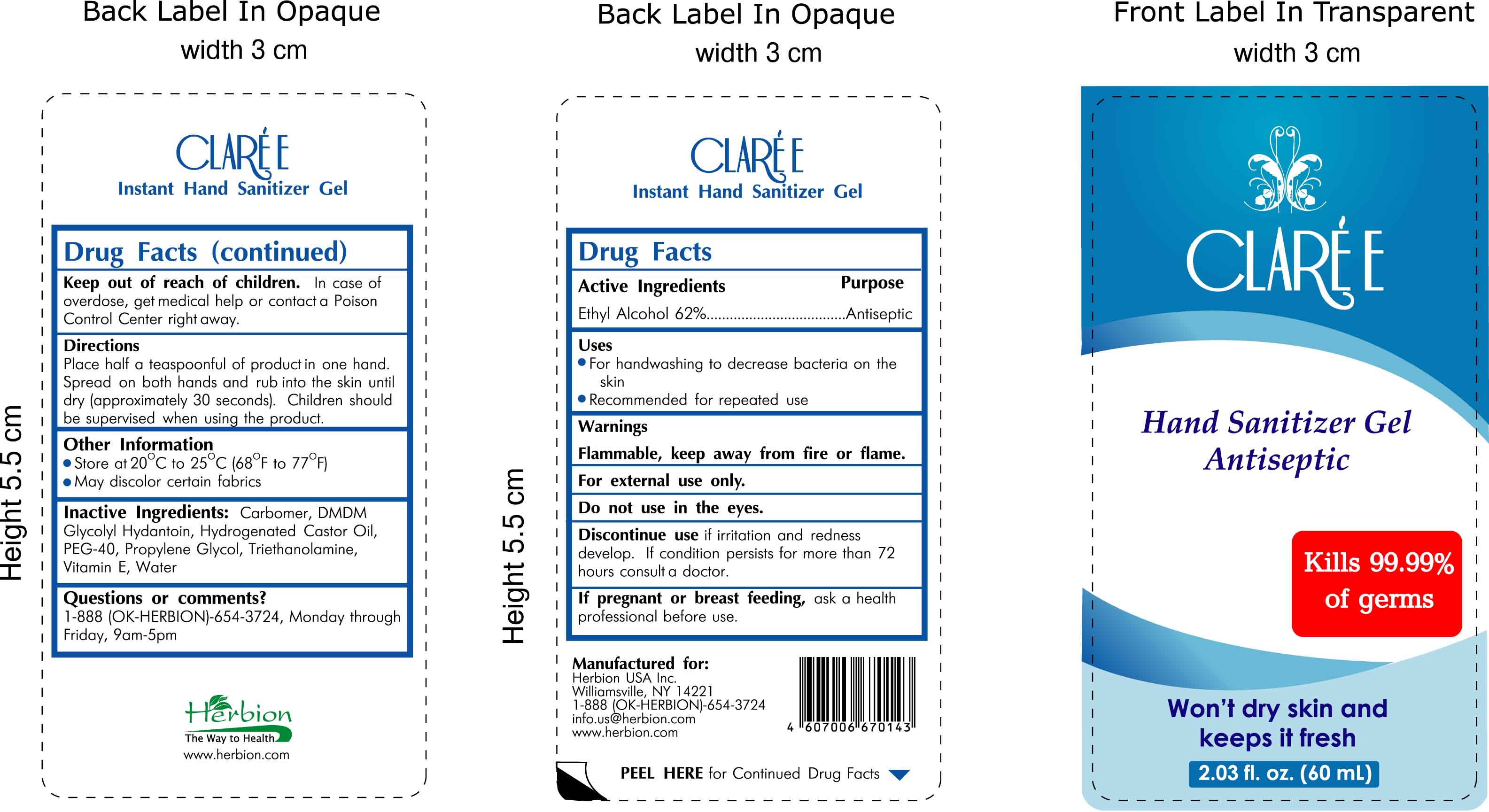 DRUG LABEL: Claree
NDC: 44237-400 | Form: GEL
Manufacturer: Herbion Pakistan (Pvt.) Ltd.
Category: otc | Type: HUMAN OTC DRUG LABEL
Date: 20100129

ACTIVE INGREDIENTS: ALCOHOL 37 mL/60 mL

Uses:

- For handwashing to decrease bacteria on the skin
- Recommended for repeated use

Directions:

Place half a teaspoonful of product in one hand. Spread on both hands and rub into the skin until dry (approximately 30 seconds).
Children should be supervised when using this product.

Warnings:

Flammable, keep away from fire or flame.

For external use only.

Do not use in the eyes.

Discontinue use if irritation and redness develop. If condition persists for more than 72 hours consult a doctor.

If pregnant or breast feeding, ask a health professional before use.

Keep out of reach of children. In case of overdose, get medical help or contact a Poison Control Center right away.

Other Information:

- Store at 20 (degrees C) to 25 (degrees C) [68 degrees F to 77 degrees F]
- May discolor certain fabrics

INACTIVE INGREDIENT

Inactive Ingredients: Carbomer, DMDM Glycolyl Hydantoin, Hydrogenated Castor Oil, PEG-40,
Propylene Glycol, Triethanolamine, Vitamin E, Water

Active Ingredients Purpose
Ethyl Alcohol 62% Antiseptic

Questions or comments?

1-888 (OK-HERBION)-654-3724, Monday through Friday, 9am-5pm

Manufactured for:
Herbion USA Inc.
Williamsville, NY 14221
1-888- (OK-HERBION)-654-3724
info.us@herbion.com
www.herbion.com

PACKAGE LABEL

Claree

Hand Sanitizer Gel

Antiseptic